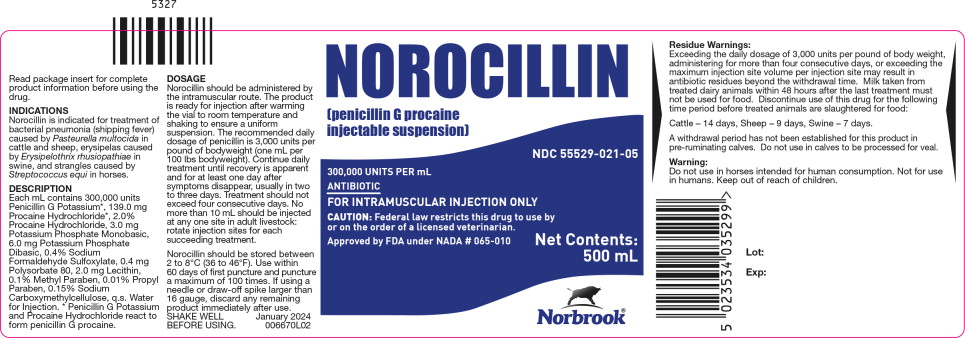 DRUG LABEL: Norocillin
NDC: 55529-021 | Form: INJECTION, SUSPENSION
Manufacturer: Norbrook Laboratories Limited
Category: animal | Type: PRESCRIPTION ANIMAL DRUG LABEL
Date: 20250127

ACTIVE INGREDIENTS: penicillin G procaine 300000 [USP'U]/1 mL
INACTIVE INGREDIENTS: penicillin G potassium; procaine hydrochloride; potassium phosphate, monobasic; potassium phosphate, dibasic; sodium formaldehyde sulfoxylate; polysorbate 80; methylparaben; water; carboxymethylcellulose sodium; lecithin, soybean

Approved by FDA under NADA # 065-010
NOROCILLIN
(penicillin G procaine injectable suspension)
For use in Cattle, Sheep, Swine and Horses.

ANTIBIOTIC

Caution: Federal law restricts this drug to use by or on the order of a licensed veterinarian.

READ ENTIRE BROCHURE CAREFULLY BEFORE USING THIS PRODUCT

Description:

Norocillin is a suspension of penicillin G procaine in 100, 250, and 500 mL multiple dose vials. Each mL is designed to provide 300,000 units of penicillin G as procaine in a stable suspension. Penicillin G procaine is an antibacterial agent which has activity against a variety of pathogenic organisms, mainly in the Gram-positive category.

Indications:

Norocillin is indicated for treatment of bacterial pneumonia (shipping fever) caused by Pasteurella multocida in cattle and sheep, erysipelas caused by Erysipelothrix rhusiopathiae in swine, and strangles caused by Streptococcus equi in horses.

Directions for Use:

A thoroughly cleaned, sterile needle and syringe should be used for each injection (needles and syringes may be sterilized in boiling water for 15 minutes).Before withdrawing the solution from the bottle, disinfect the rubber cap top with 70% alcohol. The injection site should be similarly disinfected with alcohol. Needles of 16 to 18 gauge and 1 to 1.5 inches long are adequate for intramuscular injections.

In livestock intramuscular injections should be made by directing the needle of suitable gauge and length into the fleshy part of a thick muscle, such as rump, hip, or thigh region; avoid blood vessels and major nerves. Before injecting the solution, pull back gently on the plunger.

If blood appears in the syringe, a blood vessel has been entered; withdraw the needle and select a different site.

Dosage:

Norocillin is administered by the intramuscular route. The product is ready for injection after warming the vial to room temperature and shaking to ensure a uniform suspension.

The daily dose of penicillin is 3,000 units per pound of body weight (1 mL per 100 lbs body weight). Continue daily treatment until recovery is apparent and for at least one day after symptoms disappear, usually in two to three days.

Treatment should not exceed four consecutive days.

No more than 10 mL should be injected at any one site. Rotate injection sites for each succeeding treatment.

Care of Sick Animals:

The use of antibiotics in the management of diseases is based on an accurate diagnosis and an adequate course of treatment. When properly used in the treatment of diseases caused by penicillin-susceptible organisms, most animals treated with Norocillin show a noticeable improvement within 24 to 48 hours. If improvement does not occur within this period of time, the diagnosis and course of treatment should be re-evaluated. It is recommended that the diagnosis and treatment of animal diseases be carried out by a veterinarian.

Since many diseases look alike but require different types of treatment, the use of professional veterinary and laboratory services can reduce treatment time, costs and needless losses. Good housing, sanitation and nutrition are important in the maintenance of healthy animals and are essential in the treatment of disease.

Residue Warnings:

Exceeding the daily dosage of 3,000 units per pound of body weight, administering for more than four consecutive days, or exceeding the maximum injection site volume per injection site may result in antibiotic residues beyond the withdrawal time. Milk taken from treated dairy animals within 48 hours after the last treatment must not be used for food. Discontinue use of this drug for the following time period before treated animals are slaughtered for food:

Cattle – 14 days, Sheep – 9 days, Swine – 7 days.

A withdrawal period has not been established for this product in pre-ruminating calves. Do not use in calves to be processed for veal.

Warning:

Do not use in horses intended for human consumption. Not for use in humans. Keep out of reach of children.

Precautions:

Intramuscular injection in cattle, sheep, and swine may result in a local tissue reaction which persists beyond the withdrawal period of 14 days (cattle), 9 days (sheep), or 7 days (swine). This may result in trim loss of edible tissue at slaughter.

Allergic or anaphylactic reactions, sometimes fatal, have been known to occur in animals hypersensitive to penicillin and procaine. Such reactions can occur unpredictably with varying intensity. Animals administered penicillin G procaine should be kept under close observation for at least one half hour. Should allergic or anaphylactic reactions occur, discontinue use of the product and call a veterinarian. If respiratory distress is severe, immediate injection of epinephrine or antihistamine following manufacturer's recommendations may be necessary.

As with all antibiotic preparations, use of this drug may result in overgrowth of nonsusceptible organisms, including fungi. A lack of response by the treated animal, or the development of new signs or symptoms suggest that an overgrowth of nonsusceptible organisms has occurred. In such instances, consult your veterinarian.

It is advisable to avoid giving penicillin in conjunction with bacteriostatic drugs such as tetracyclines.

To report a suspected adverse reaction call 1-866-591-5777.

Storage Conditions:

Norocillin should be stored between 2 to 8°C (36 to 46°F). Use within 60 days of first puncture and puncture a maximum of 100 times. 250 and 500 mL vials: If using a needle or draw-off spike larger than 16 gauge, discard any remaining product immediately after use.

Made in the UK.

Norbrook Laboratories Limited
Newry, BT35 6QQ,
Co. Down, Northern Ireland

February 2022

112670I02

Norbrook ®

Principal Display Panel – 500 mL Vial Label

NOROCILLIN

[penicillin G procaine
injectable suspension]

NDC 55529-021-05

300,000 UNITS PER mL

ANTIBIOTIC

FOR INTRAMUSCULAR INJECTION ONLY

CAUTION: Federal law restricts this drug to use by
or on the order of a licensed veterinarian.

Approved by FDA under NADA # 065-010

Net Contents:
500 mL

Norbrook®